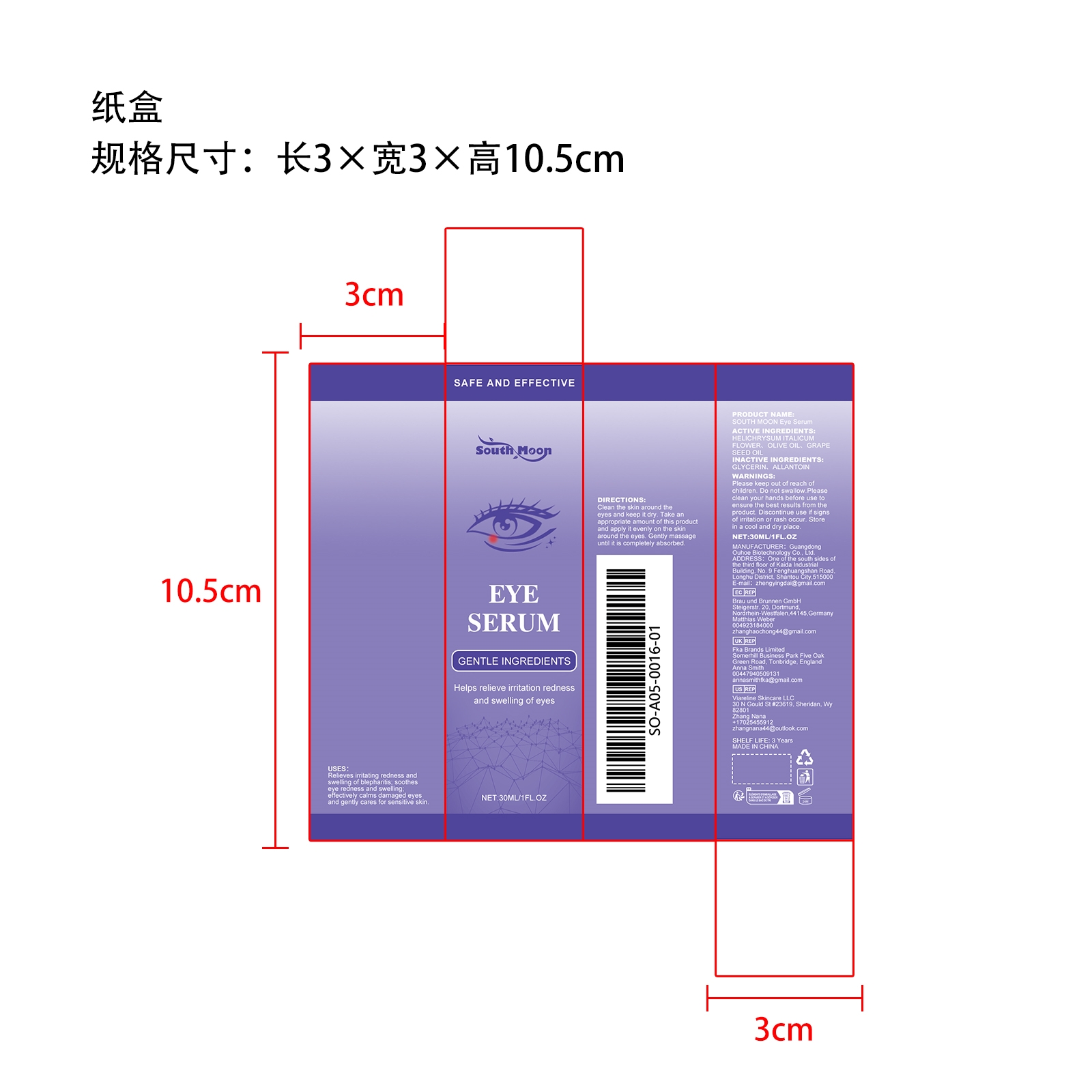 DRUG LABEL: SOUTH MOON Eye Serum
NDC: 84744-068 | Form: LIQUID
Manufacturer: Guangdong Ouhoe Biotechnology Co., Ltd.
Category: otc | Type: HUMAN OTC DRUG LABEL
Date: 20241028

ACTIVE INGREDIENTS: HELICHRYSUM ITALICUM FLOWER 9 mg/30 mg; GRAPE SEED OIL 4.5 mg/30 mg; OLIVE OIL 3 mg/30 mg
INACTIVE INGREDIENTS: GLYCERIN 4.5 mg/30 mg; ALLANTOIN 9 mg/30 mg

ACTIVE INGREDIENTS

HELICHRYSUM ITALICUM FLOWER，OLIVE OIL，GRAPE SEED OIL

PURPOSE

Relieves irritating redness and swelling of blepharitis; soothes eye redness and swelling effectively calms damaged eyes and gently cares for sensitive skin.

USE

Clean the skin around the eyes and keep it dry. Take an appropriate amount of this product and apply it evenly on the skin around the eyes. Gently massage until it is completely absorbed.

WARNINGS

Please keep out of reach of children. Do not swallow.Please clean your hands before use to ensure the best results from the product. Discontinue use if signs of irritation or rash occur. Store in a cool and dry place.

STOP USE

Discontinue use if signs of irritation or rash occur.

DO NOT USE

Discontinue use if signs of irritation or rash occur.

KEEP OUT OF REACH OF CHILDREN

Please keep out of reach of children. Do not swallow.

STORAGE AND HANDLING

Store in a cool and dry place.

INACTIVE INGREDIENT

GLYCERIN、ALLANTOIN